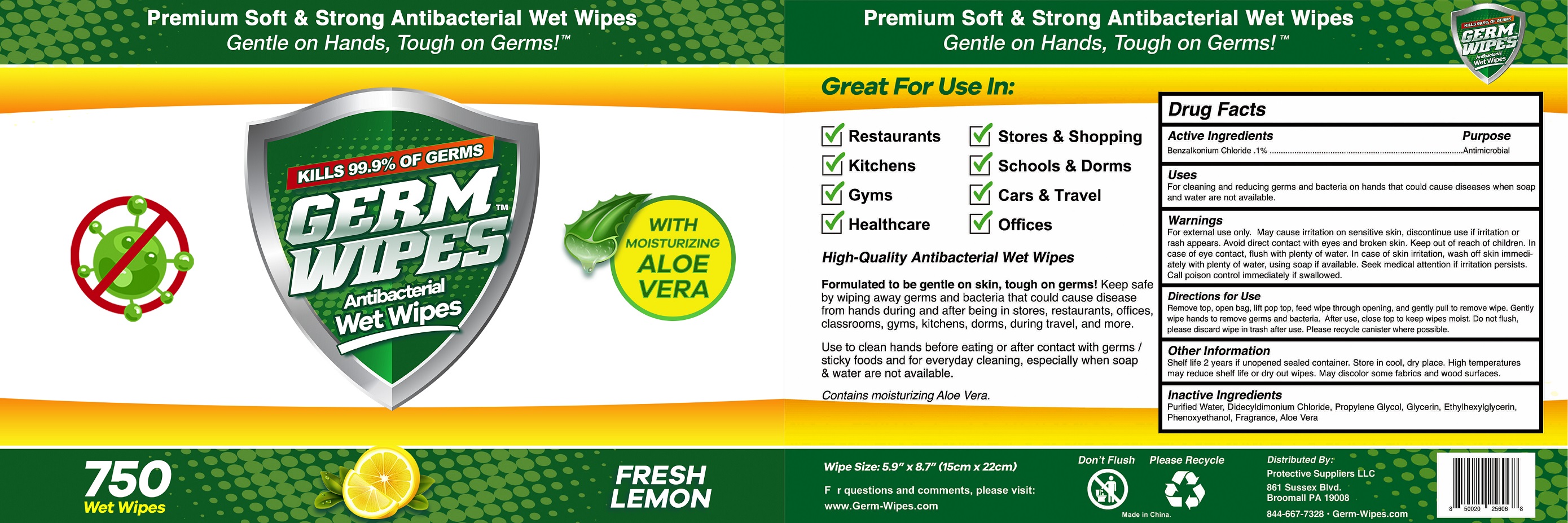 DRUG LABEL: Germ Wipes
NDC: 75662-751 | Form: CLOTH
Manufacturer: Ningbo Chenxing Daily Necessities Co., Ltd.
Category: otc | Type: HUMAN OTC DRUG LABEL
Date: 20200817

ACTIVE INGREDIENTS: BENZALKONIUM CHLORIDE 0.1 g/100 g
INACTIVE INGREDIENTS: GLYCERIN; FRAGRANCE LEMON ORC2001060; ALOE VERA LEAF; DIDECYLDIMONIUM CHLORIDE; WATER; PROPYLENE GLYCOL; PHENOXYETHANOL; ETHYLHEXYLGLYCERIN

75662-751 Germ Wipes/Germ Wipes Ningbo Chenxing Daily Necessities Co., Ltd.

Active Ingredient(s)

Benzalkonium Chloride 0.1%. Purpose: Antimicrobial

Purpose

antimicrobial, Wet Wipes

Use

For cleaning and reducing germs and bacteria on hand that could cause diseases when soap and water are not available.

Warnings

For external use only. May cause irritation on sensitive skin,discontinue use if irritation or rash appears.Avoid direct contact with eyes and broken skin. Keep out of reach of children. In case of eye contact , flush with plenty of water. In case of skin irritation, wash off skin immediatelly with plenty of water, using soap if available. Seek medical attention if irritation persists.Call poison control immediately if swallowed.

Do not use

- in children less than 2 months of age
- on open skin wounds

When using this product keep out of eyes, ears, and mouth. In case of contact with eyes, rinse eyes thoroughly with water.
Stop use and ask a doctor if irritation or rash occurs. These may be signs of a serious condition.
Keep out of reach of children. If swallowed, get medical help or contact a Poison Control Center right away.

Stop use and ask a doctor if irritation or rash occurs. These may be signs of a serious condition.

Keep out of reach of children. If swallowed, get medical help or contact a Poison Control Center right away.

Directions

Remove top, open bag,lift pop top,feed wipe through opening, and gently pull to remove wipe. Gently wipe hands to remove germs and becteria. After use, close top to keep wipes moist. Do not flush, please discard wipe in trash after use. Please recycle canister where possible.

Other information

Shelf life 2 years if unopened sealed container. Store in cool, dry place. High temperatures may reduce shelf life or dry out wipes. May discolor some fabrics and wood surface.

Inactive ingredients

Purified water, Didecyldimonium Chloride, Propylene Glycol, Glycerin, Ethylhexyl Glycerin,Phenoxyethanol,Fragrance,Aloe Vera

SPL UNCLASSIFIED SECTION

Premium Soft & Strong Antibacterial Wet Wipes

Gentle on Hands, Tough on Germs!

KILLS 99.9% OF GERMS

WITH MOISTURIZING ALOE VERA

750 Wet Wipes

FRESH LEMON

Great For Use In: Restaurants,Stores & Shopping, Kitchens, Schools & Dorms, Gyms, Cars & Travel, Healthcare, Offices.

High-Quality Antibacterial Wet Wipes

Formulated to be gentle on skin, tough on germs! Keep safe by wiping away germs and bacteria that could cause disease from hands during and after being in stores, restaurants, offices, classrooms, gyms, kitchens, dorms, during travel, and more.

Use to clean hands before eating or after contact with germs / sticky foods and for everyday cleaning, especially when soap & water are not available.

Contains moisturizing Aloe Vera.

Package Label - Principal Display Panel

750 Wet Wipes NDC:75662-751-01